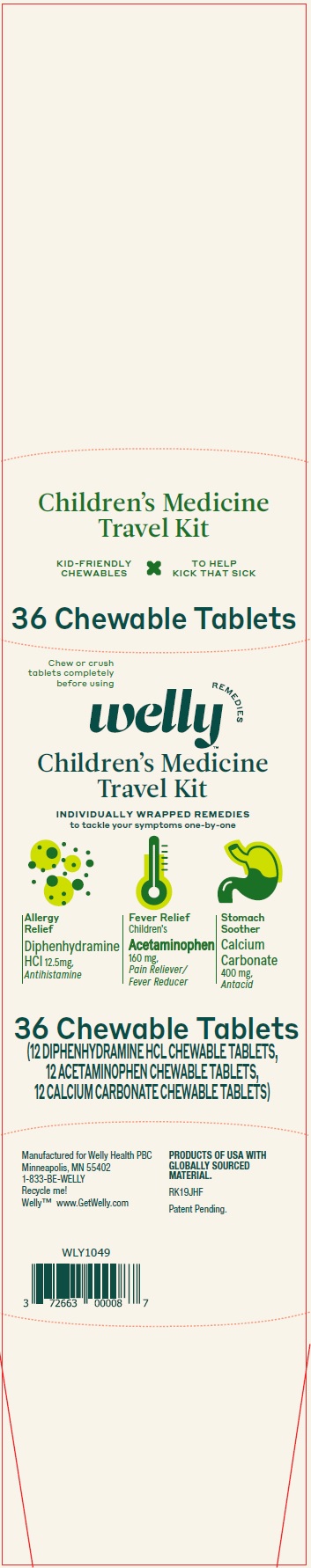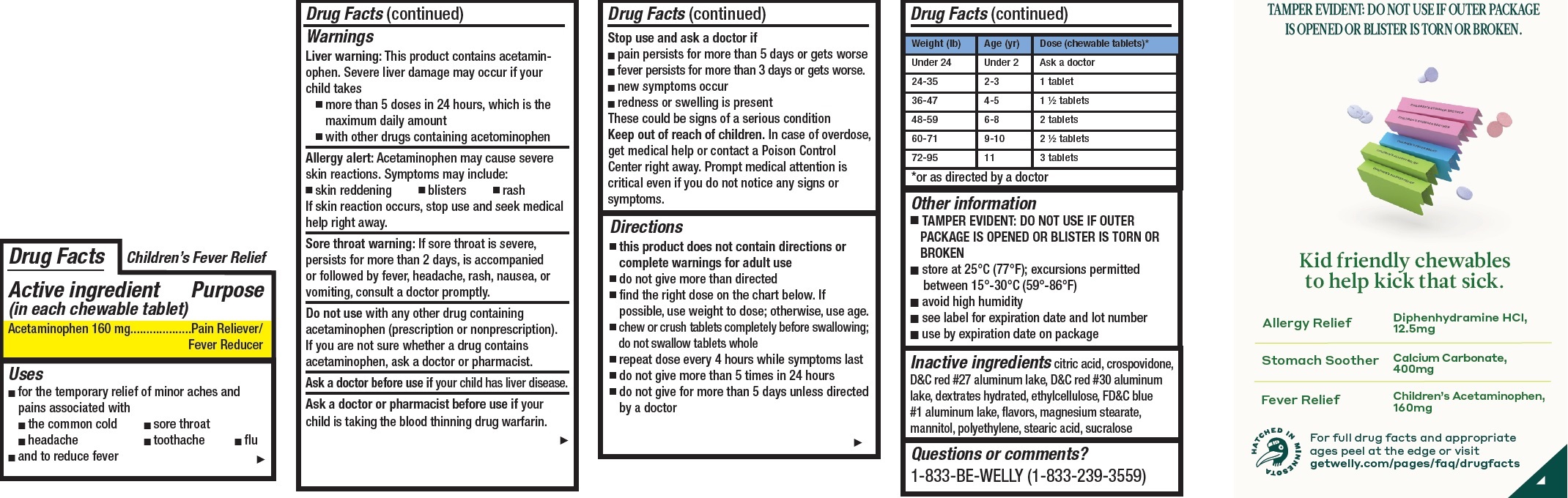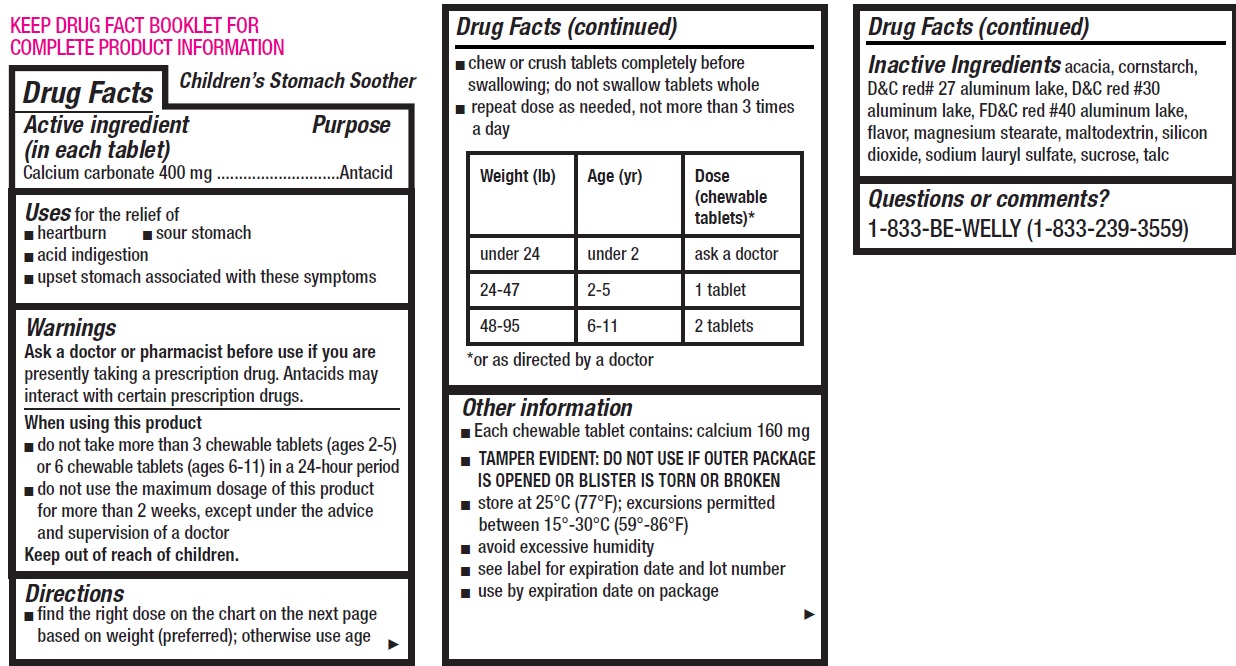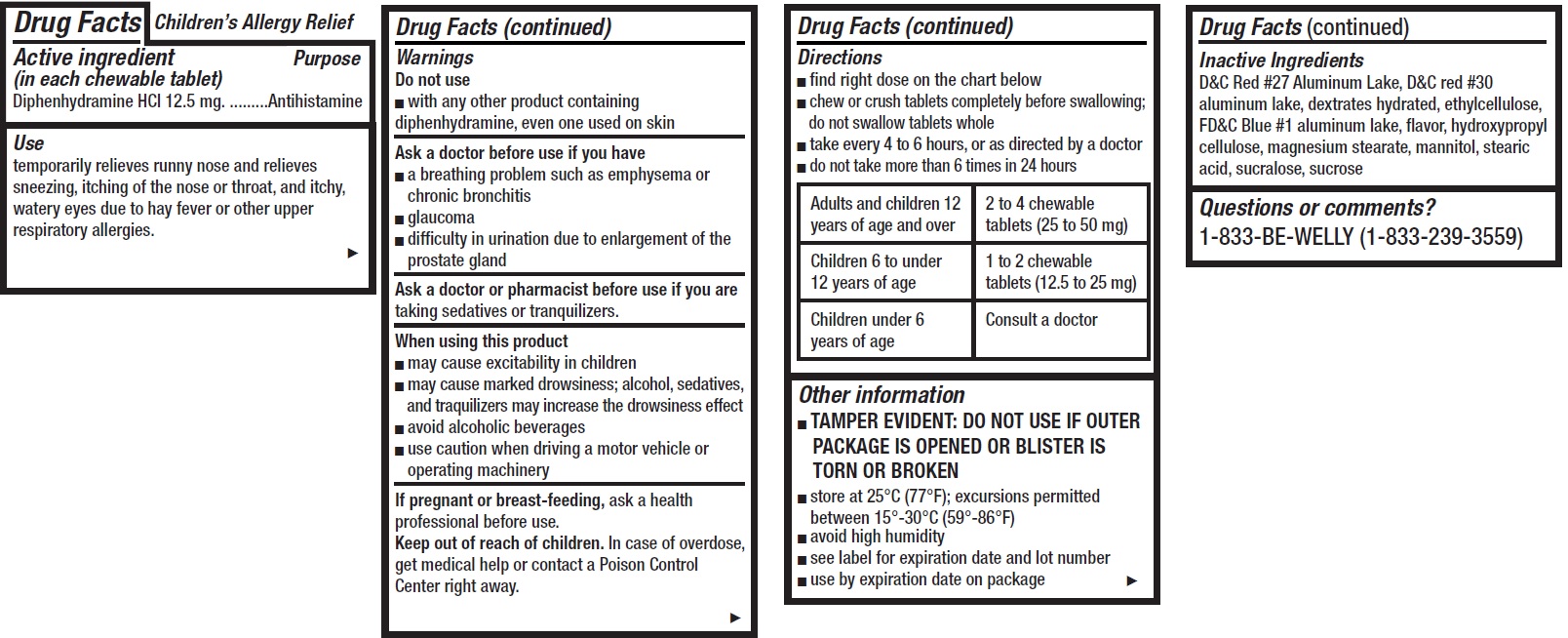 DRUG LABEL: Welly Childrens Travel Medicine
NDC: 72663-203 | Form: KIT | Route: ORAL
Manufacturer: Welly Health PBC
Category: otc | Type: HUMAN OTC DRUG LABEL
Date: 20200415

ACTIVE INGREDIENTS: ACETAMINOPHEN 160 mg/1 1; CALCIUM CARBONATE 400 mg/1 1; DIPHENHYDRAMINE HYDROCHLORIDE 12.5 mg/1 1
INACTIVE INGREDIENTS: CITRIC ACID MONOHYDRATE; CROSPOVIDONE; D&C RED NO. 27; D&C RED NO. 30; ETHYLCELLULOSE, UNSPECIFIED; FD&C BLUE NO. 1 ALUMINUM LAKE; METHYL SALICYLATE; MAGNESIUM STEARATE; MANNITOL; HIGH DENSITY POLYETHYLENE; STEARIC ACID; SUCRALOSE; ACACIA; STARCH, CORN; D&C RED NO. 27 ALUMINUM LAKE; D&C RED NO. 30; FD&C RED NO. 40; METHYL SALICYLATE; MAGNESIUM STEARATE; MALTODEXTRIN; SILICON DIOXIDE; SODIUM LAURYL SULFATE; SUCROSE; TALC; D&C RED NO. 27 ALUMINUM LAKE; D&C RED NO. 30; ETHYLCELLULOSE, UNSPECIFIED; FD&C BLUE NO. 1 ALUMINUM LAKE; METHYL SALICYLATE; HYDROXYPROPYL CELLULOSE, UNSPECIFIED; MAGNESIUM STEARATE; MANNITOL; STEARIC ACID; SUCRALOSE; SUCROSE

Welly Children's Travel Medicine Kit

Active ingredient (in each chewable tablet)

Acetaminophen 160 mg

Purpose

Pain Reliever/ Fever Reducer

Uses

- for the temporary relief of minor aches and pains associated with
- the common cold
- sore throat
- headache
- toothache
- flu
- and to reduce fever

Warnings

Liver warning: This product contains acetaminophen. Severe liver damage may occur if your child takes

- more than 5 doses in 24 hours, which is the maximum daily amount
- with other drugs containing acetominophen

Allergy alert: Acetaminophen may cause severe skin reactions. Symptoms may include:

- skin reddening
- blisters
- rash

If skin reaction occurs, stop use and seek medical help right away.

Sore throat warning: If sore throat is severe, persists for more than 2 days, is accompanied or followed by fever, headache, rash, nausea, or vomiting, consult a doctor promptly.

Do not use

with any other drug containing acetaminophen (prescription or nonprescription). If you are not sure whether a drug contains acetaminophen, ask a doctor or pharmacist.

Ask a doctor before use if

your child has liver disease.

Ask a doctor or pharmacist before use if

your child is taking the blood thinning drug warfarin.

Stop use and ask a doctor if

- pain persists for more than 5 days or gets worse
- fever persists for more than 3 days or gets worse.
- new symptoms occur
- redness or swelling is present

These could be signs of a serious condition

Keep out of reach of children.

In case of overdose, get medical help or contact a Poison Control Center right away. Prompt medical attention is critical even if you do not notice any signs or symptoms.

Directions

- this product does not contain directions or complete warnings for adult use
- do not give more than directed
- find the right dose on the chart below. If possible, use weight to dose; otherwise, use age.
- chew or crush tablets completely before swallowing; do not swallow tablets whole
- repeat dose every 4 hours while symptoms last
- do not give more than 5 times in 24 hours
- do not give for more than 5 days unless directed by a doctor

Weight (lb) | Age (yr) | Dose (chewable tablets)*
Under 24 | Under 2 | Ask a doctor
24-35 | 2-3 | 1 tablet
36-47 | 4-5 | 1 1/2 tablets
48-59 | 6-8 | 2 tablets
60-71 | 9-10 | 2 1/2 tablets
72-95 | 11 | 3 tablets

*or as directed by a doctor

Other information

TAMPER EVIDENT: DO NOT USE IF OUTER PACKAGE IS OPENED OR BLISTER IS TORN OR BROKEN

- store at 25°C (77°F); excursions permitted between 15°-30°C (59°-86°F)
- avoid high humidity
- see label for expiration date and lot number
- use by expiration date on package

Inactive ingredients

citric acid, crospovidone, D&C red #27 aluminum lake, D&C red #30 aluminum lake, dextrates hydrated, ethylcellulose, FD&C blue #1 aluminum lake, flavors, magnesium stearate, mannitol, polyethylene, stearic acid, sucralose

Questions or comments?

1-833-BE-WELLY (1-833-239-3559)

Active ingredient (in each tablet)

Calcium carbonate 400 mg

Purpose

Antacid

Uses

for the relief of

- heartburn
- sour stomach
- acid indigestion
- upset stomach associated with these symptoms

Warnings

Ask a doctor or pharmacist before use if you are

presently taking a prescription drug. Antacids may interact with certain prescription drugs.

When using this product

- do not take more than 3 chewable tablets (ages 2-5) or 6 chewable tablets (ages 6-11) in a 24-hour period
- do not use the maximum dosage of this product for more than 2 weeks, except under the advice and supervision of a doctor

Directions

- find the right dose on the chart on the next page based on weight (preferred); otherwise use age
- chew or crush tablets completely before swallowing; do not swallow tablets whole
- repeat dose as needed, not more than 3 times a day

Weight (lb) | Age (yr) | Dose (chewable tablets)*
under 24 | under 2 | ask a doctor
24-47 | 2-5 | 1 tablet
48-95 | 6-11 | 2 tablets

*or as directed by a doctor

Other information

- Each chewable tablet contains: calcium 160 mg
- TAMPER EVIDENT: DO NOT USE IF OUTER PACKAGE IS OPENED OR BLISTER IS TORN OR BROKEN
- store at 25°C (77°F); excursions permitted between 15°-30°C (59°-86°F)
- avoid excessive humidity
- see label for expiration date and lot number
- use by expiration date on package

Inactive Ingredients

acacia, cornstarch, D&C red# 27 aluminum lake, D&C red #30 aluminum lake, FD&C red #40 aluminum lake, flavor, magnesium stearate, maltodextrin, silicon dioxide, sodium lauryl sulfate, sucrose, talc

Questions or comments?

1-833-BE-WELLY (1-833-239-3559)

Active ingredient (in each chewable tablet)

Diphenhydramine HCI 12.5 mg

Purpose

Antihistamine

Use

temporarily relieves runny nose and relieves sneezing, itching of the nose or throat, and itchy, watery eyes due to hay fever or other upper respiratory allergies.

Warnings

Do not use

- with any other product containing diphenhydramine, even one used on skin

Ask a doctor before use if you have

- a breathing problem such as emphysema or chronic bronchitis
- glaucoma
- difficulty in urination due to enlargement of the prostate gland

Ask a doctor or pharmacist before use if you are

taking sedatives or tranquilizers.

When using this product

- may cause excitability in children
- may cause marked drowsiness; alcohol, sedatives, and traquilizers may increase the drowsiness effect
- avoid alcoholic beverages
- use caution when driving a motor vehicle or operating machinery

If pregnant or breast-feeding,

ask a health professional before use.

Keep out of reach of children.

In case of overdose, get medical help or contact a Poison Control Center right away.

Directions

- find right dose on the chart below
- chew or crush tablets completely before swallowing; do not swallow tablets whole
- take every 4 to 6 hours, or as directed by a doctor
- do not take more than 6 times in 24 hours

Adults and children 12 years of age and over | 2 to 4 chewable tablets (25 to 50 mg)
Children 6 to under 12 years of age | 1 to 2 chewable tablets (12.5 to 25 mg)
Children under 6 years of age | Consult a doctor

Other information

- TAMPER EVIDENT: DO NOT USE IF OUTER PACKAGE IS OPENED OR BLISTER IS TORN OR BROKEN
- store at 25°C (77°F); excursions permitted between 15°-30°C (59°-86°F)
- avoid high humidity
- see label for expiration date and lot number
- use by expiration date on package

Inactive Ingredients

D&C Red #27 Aluminum Lake, D&C red #30 aluminum lake, dextrates hydrated, ethylcellulose, FD&C Blue #1 aluminum lake, flavor, hydroxypropyl cellulose, magnesium stearate, mannitol, stearic acid, sucralose, sucrose

Questions or comments?

1-833-BE-WELLY (1-833-239-3559)